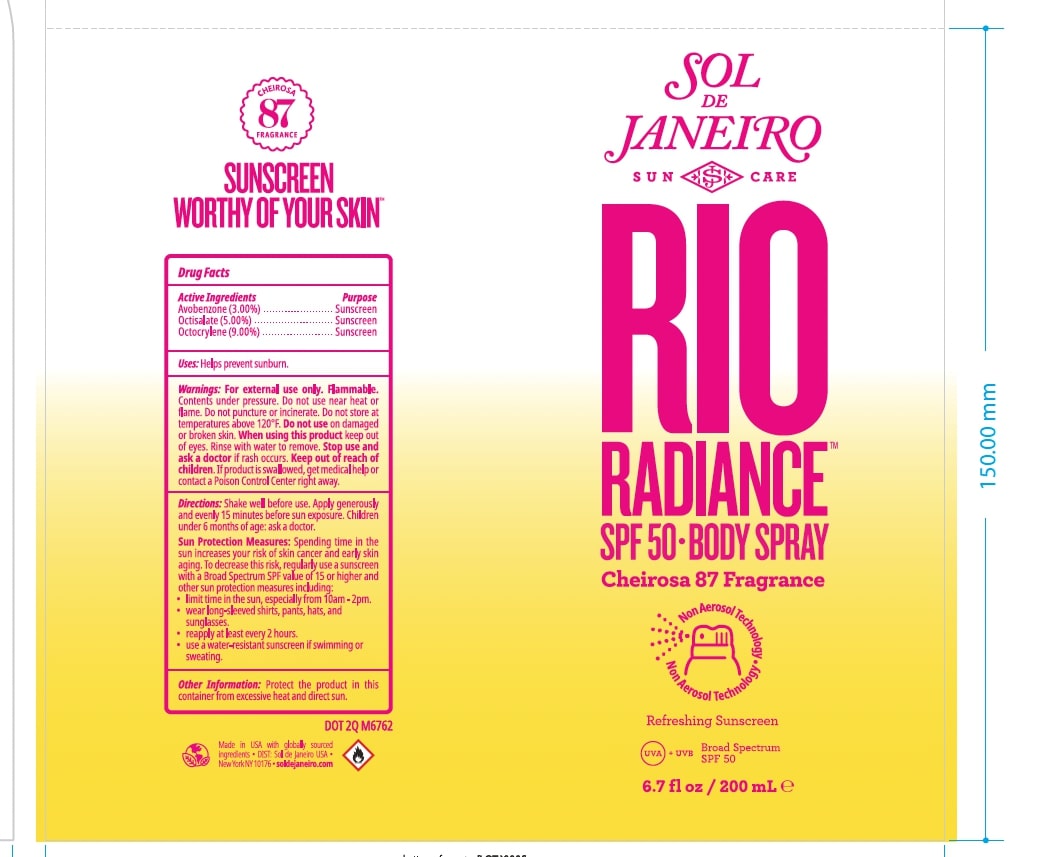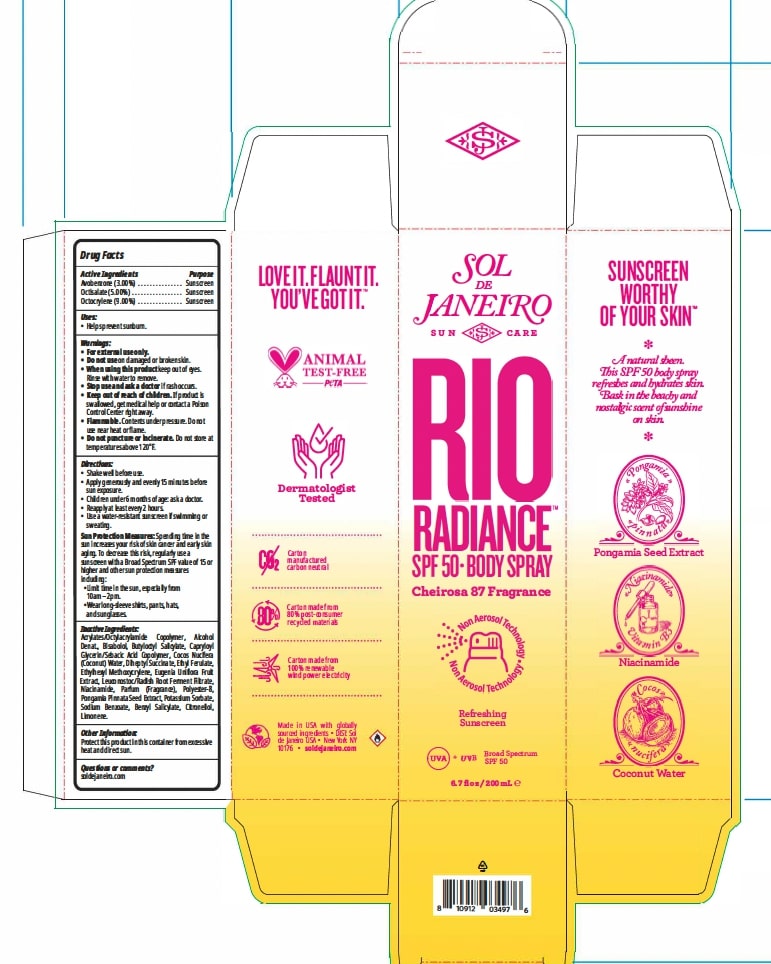 DRUG LABEL: Rio Radiance SPF 50 BodySpray
NDC: 83982-1001 | Form: AEROSOL, SPRAY
Manufacturer: Sol de Janeiro USA, Inc
Category: otc | Type: HUMAN OTC DRUG LABEL
Date: 20240402

ACTIVE INGREDIENTS: AVOBENZONE 3 g/100 mL; OCTOCRYLENE 9 g/100 mL; OCTISALATE 5 g/100 mL
INACTIVE INGREDIENTS: EUGENIA UNIFLORA FRUIT; LEUCONOSTOC/RADISH ROOT FERMENT FILTRATE; SODIUM BENZOATE; ALCOHOL; POLYESTER-8 (1400 MW, CYANODIPHENYLPROPENOYL CAPPED); DIHEPTYL SUCCINATE; CAPRYLOYL GLYCERIN/SEBACIC ACID COPOLYMER (2000 MPA.S); POTASSIUM SORBATE; ACRYLATES/OCTYLACRYLAMIDE COPOLYMER (40000 MW); ETHYL FERULATE; NIACINAMIDE; LEVOMENOL; BUTYLOCTYL SALICYLATE; ETHYLHEXYL METHOXYCRYLENE; PONGAMIA PINNATA SEED; COCONUT WATER

Drug Facts

Active Ingredients Purpose

Avobenzone (3.00%)......Sunscreen

Octisalate (5.00%)..........Sunscreen

Octocrylene (9.00%).......Sunscreen

Dosage: Evenly and generously apply to skin.

Administration: Topical

Warnings:
• For external use only.
• Do not use on damaged or broken skin.
• When using this product keep out of eyes. Rinse with water to
remove.
• Stop use and ask a doctor if rash occurs.
• Keep out of reach of children. If product is swallowed, get
medical help or contact a Poison Control Center right away.

• Flammable. Contents under pressure. Do not use near heat or flame.

• Do not puncture or incinerate. Do not store at temperatures above 120°F.

Sun Protection Measures: Spending time in the sun increases

your risk of skin cancer and early skin aging. To decrease this risk,

regularly use a sunscreen with a Broad Spectrum SPF value of 15 or

higher and other sun protection measures including:

• Limit time in the sun, especially from 10am - 2pm.

• Wear long-sleeved shirts, pants, hats, and sunglasses.

INACTIVE INGREDIENT

Acrylates/Octylacrylamide Copolymer, Alcohol Denat., Bisabolol, Butyloctyl Salicylate, Capryloyl Glycerin/Sebacic Acid Copolymer, Cocos Nucifera (Coconut) Water, Diheptyl Succinate, Ethyl Ferulate, Ethylhexyl Methoxycrylene, Eugenia Uniflora Fruit Extract, Leuconostoc/Radish Root Ferment Filtrate, Niacinamide, Parfum (Fragrance), Polyester-8, Pongamia Pinnata Seed Extract, Potassium Sorbate, Sodium Benzoate, Benzyl Salicylate, Citronellol, Limonene.

Uses:

• Helps prevent sunburn.

Directions:

• Apply generously and evenly 15 minutes before sun exposure.
• Children under 6 months of age: ask a doctor.
• Reapply at least every 2 hours.
• Use a water-resistant sunscreen if swimming or sweating.

Keep out of reach of children.

PURPOSE

Sunscreen